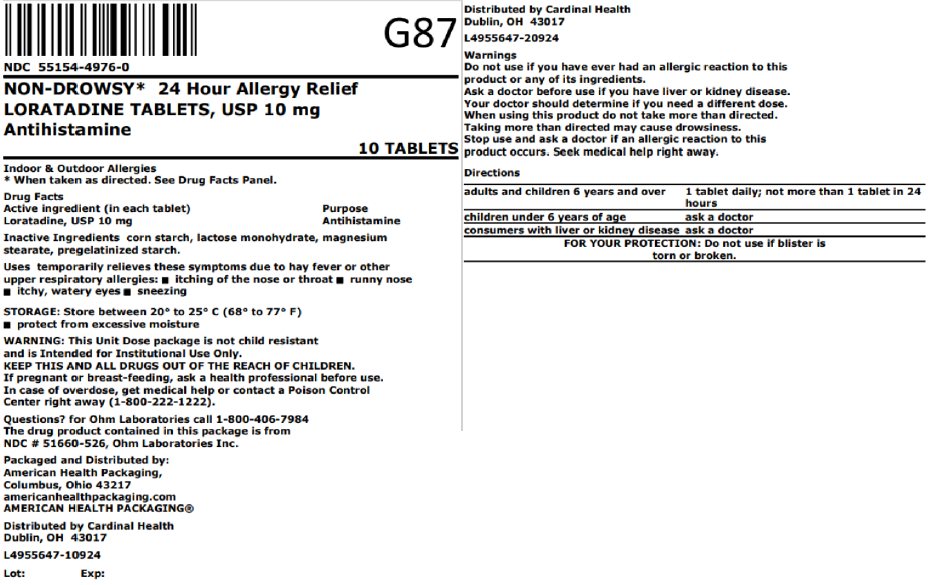 DRUG LABEL: Loratadine
NDC: 55154-4976 | Form: TABLET
Manufacturer: Cardinal Health 107, LLC
Category: otc | Type: HUMAN OTC DRUG LABEL
Date: 20251020

ACTIVE INGREDIENTS: LORATADINE 10 mg/1 1
INACTIVE INGREDIENTS: STARCH, CORN; LACTOSE MONOHYDRATE; MAGNESIUM STEARATE

Loratadine Tablets, USP Antihistamine
Drug Facts

Active ingredient (in each tablet)

Loratadine USP, 10 mg

Purpose

Antihistamine

Uses

temporarily relieves these symptoms due to hay fever or other upper respiratory allergies:

- itching of the nose or throat
- runny nose
- itchy, watery eyes
- sneezing

Warnings

Do not use

if you have ever had an allergic reaction to this product or any of its ingredients.

Ask a doctor before use if you have

liver or kidney disease. Your doctor should determine if you need a different dose.

When using this product

do not take more than directed. Taking more than directed may cause drowsiness.

Stop use and ask a doctor if

an allergic reaction to this product occurs. Seek medical help right away.

If pregnant or breast-feeding,

ask a health professional before use.

Keep out of reach of children.

In case of overdose, get medical help or contact a Poison Control Center right away (1-800-222-1222).

Directions

adults and children 6 years and over | 1 tablet daily; not more than 1 tablet in 24 hours
children under 6 years of age | ask a doctor
consumers with liver or kidney disease | ask a doctor

Other Information

- store between 20° to 25°C (68° to 77°F)
- protect from excessive moisture
- FOR YOUR PROTECTION: Do not use if blister is torn or broken.

Overbagged with 10 tablets per bag, NDC 55154-4976-0

WARNING: This Unit Dose package is not child resistant and is Intended for Institutional Use Only. Keep this and all drugs out of the reach of children.

Inactive Ingredients

Corn starch, lactose monohydrate, magnesium stearate, pregelatinized starch

Questions?

for Ohm Laboratories call 1-800-406-7984

The drug product contained in this package is from Ohm Laboratories Inc.

Packaged and Distributed by:
American Health Packaging, Columbus, Ohio 43217

Distributed By:

Cardinal Health

Dublin, OH 43017

L4955647-10924 / L4955647-20924

801697

0224801/0119

Principal Display Panel

NDC 55154-4976-0

NON-DROWSY* 24 Hour Allergy Relief

LORATADINE TABLETS, USP 10 mg

Antihistamine

10 TABLETS